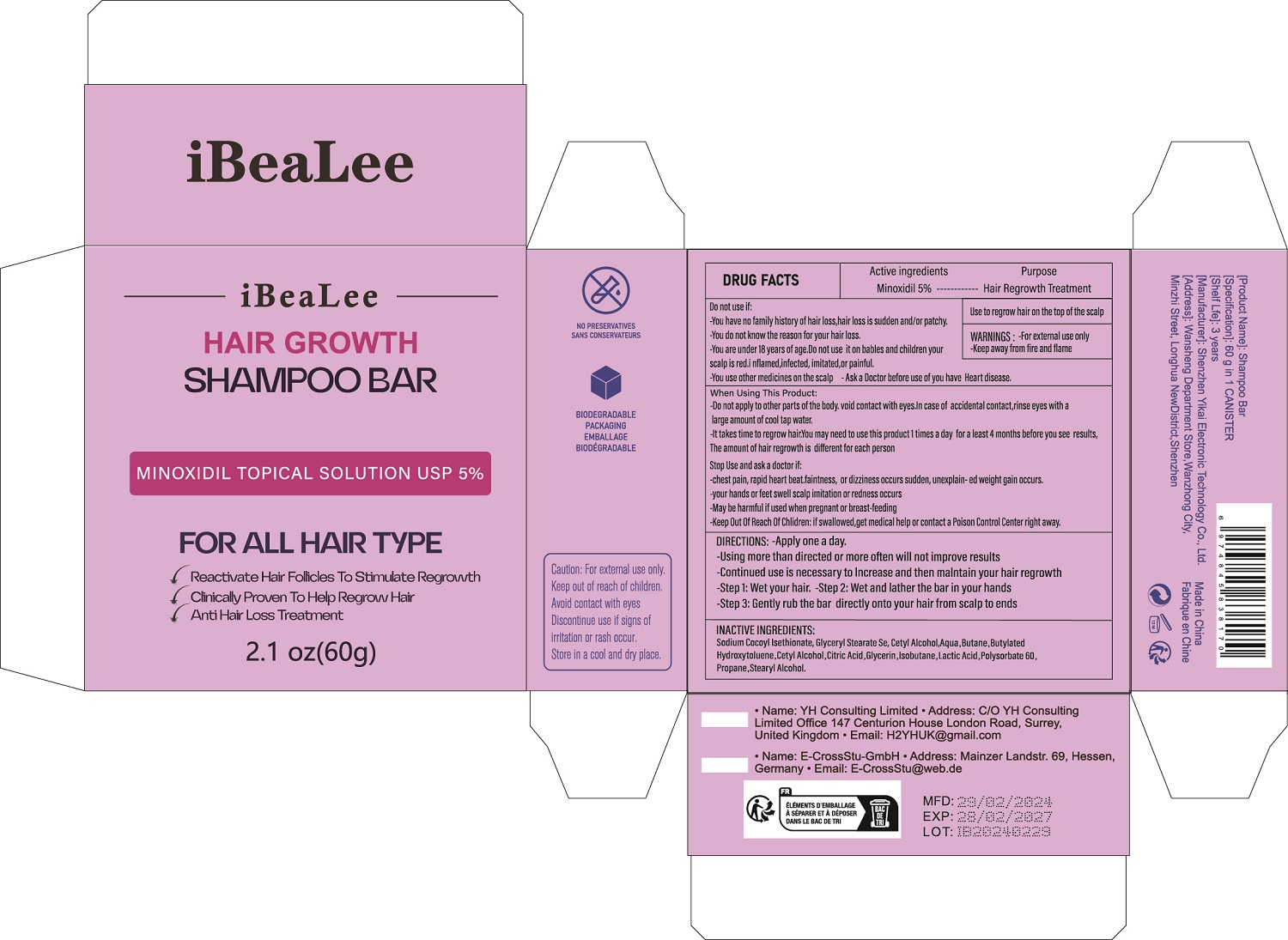 DRUG LABEL: ShampooBar
NDC: 84117-002 | Form: CREAM
Manufacturer: Shenzhen Hengkaifeng Commerce and Trade Co., Ltd
Category: otc | Type: HUMAN OTC DRUG LABEL
Date: 20240309

ACTIVE INGREDIENTS: CASTOR OIL 100 mg/5 g
INACTIVE INGREDIENTS: WATER; BUTANE; POLYSORBATE 60; ISOBUTANE; STEARYL ALCOHOL; MINOXIDIL; PROPANE; BUTYLATED HYDROXYTOLUENE; GLYCERIN; CETYL ALCOHOL; LACTIC ACID; CITRIC ACID MONOHYDRATE

ACTIVE INGREDIENT

Castor Oil 5%

Purpose

Hair Regrowth Treatment

Use

Use to regrow hair on the top of the scalp

Warnings

-For external use only
-Keep away from fire and flame

Do not use

-You have no family history of hair
loss,hair loss is sudden and/or patchy.
-You do not know the reason for your
hair loss.
-You are under 18 years of age.Do not use
it on bables and children
your scalp is red.inflamed,infected,
imitated,or painful.
-You use other medicines on the scalp
-Ask a Doctor before use of you have
Heart disease.

When Using

-Do not apply to other parts of the body. void contact with eyes.In case of accidental contact,rinse eyes with a large amount of cool tap water.
-It takes time to regrow hair.You may need to use this product 2 times a day for a least 4 months before you see results,The amount of hair regrowth is different for each person

Stop Use

-chest pain, rapid heart beat.faintness, or dizziness occurs sudden, unexplained weight gain occurs.
-your hands or feet swell scalp imitation or redness occurs
-May be harmful if used when pregnant or breast-feeding
-Keep Out Of Reach Of Chlidren: if swallowed,get medical help or contact a Poison Control Center right away.

Keep Oot Of Reach Of Children

Directions

-Apply twice a day. Once in the morning and another time in the evening before bed
-Spray directly on top of the scalp in the area to be treated
-Using more than directed or more often will not improve results
-Continued use is necessary to lncrease and then malntain your hair regrowth
-Discontinuing use may result in hair loss

Inactive ingredients

Aqua,Butane,Butylated Hydroxytoluene,Cetyl Alcohol,Citric Acid,Glycerin,Minoxidil,
Isobutane,Lactic Acid,Polysorbate 60,Propane,Stearyl Alcohol.